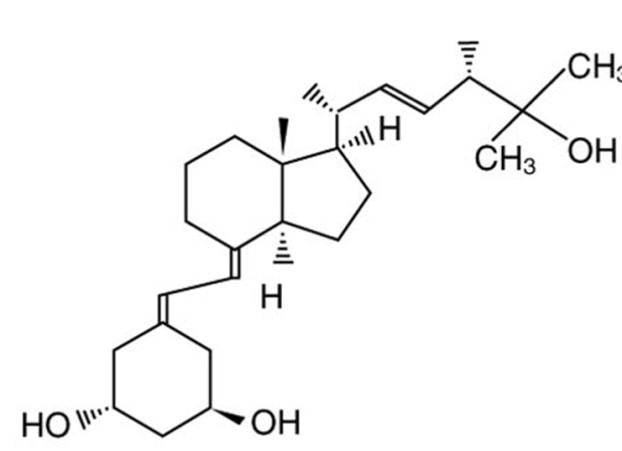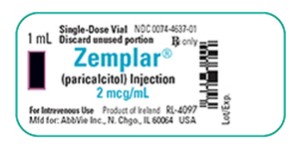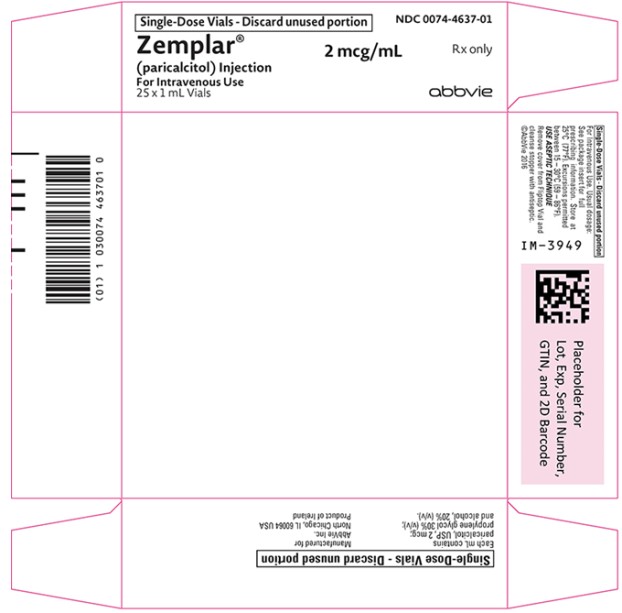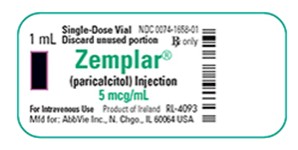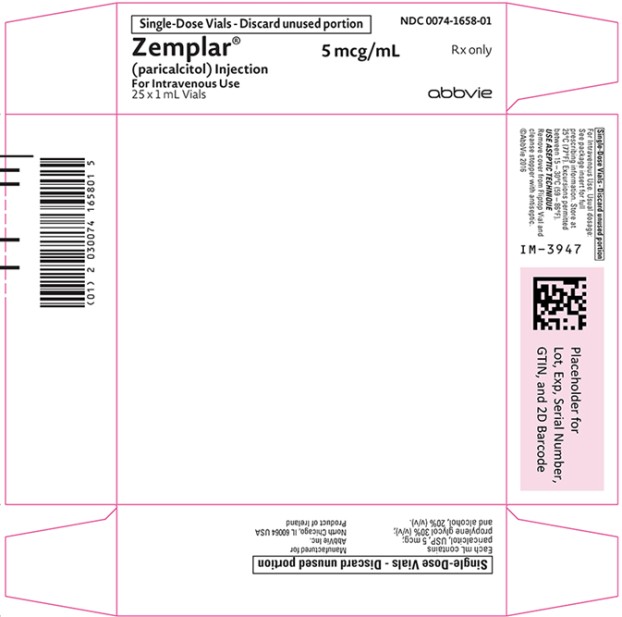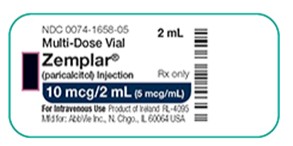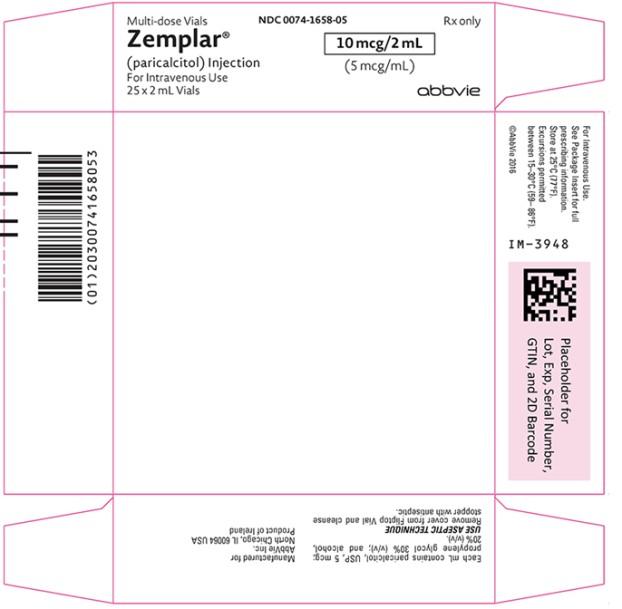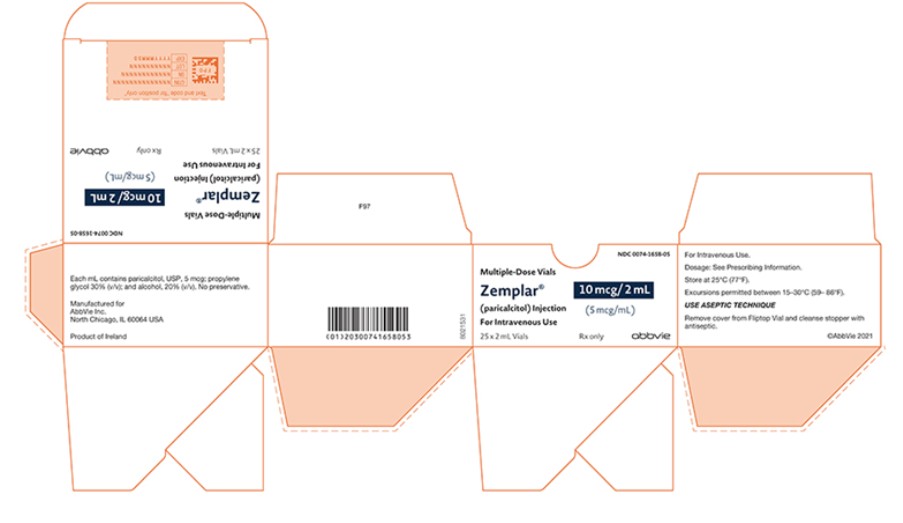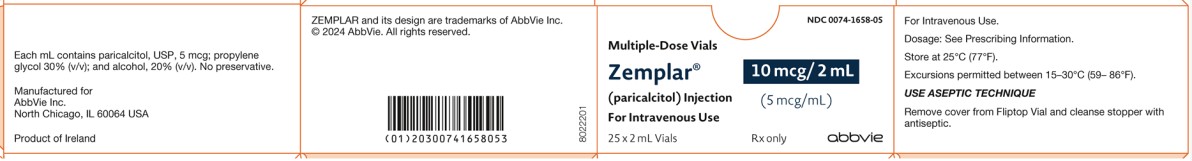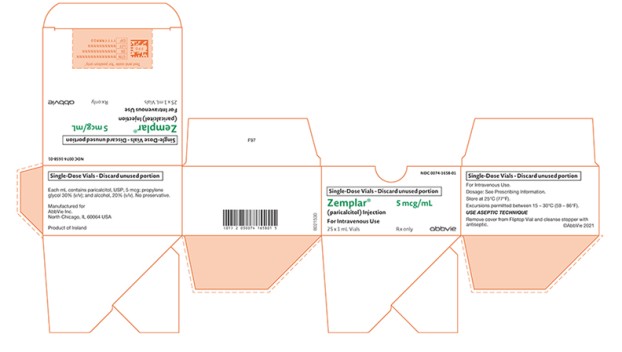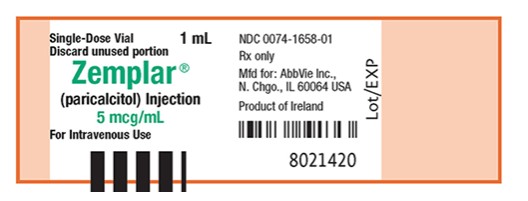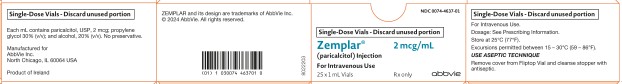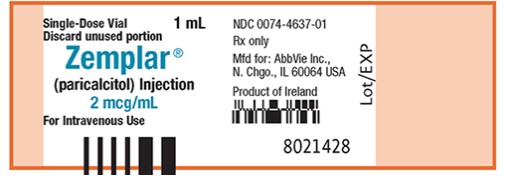 DRUG LABEL: Zemplar
NDC: 0074-4637 | Form: INJECTION, SOLUTION
Manufacturer: AbbVie Inc.
Category: prescription | Type: HUMAN PRESCRIPTION DRUG LABEL
Date: 20240801

ACTIVE INGREDIENTS: PARICALCITOL 2 ug/1 mL
INACTIVE INGREDIENTS: PROPYLENE GLYCOL; ALCOHOL; WATER

HIGHLIGHTS OF PRESCRIBING INFORMATION

These highlights do not include all the information needed to use ZEMPLAR safely and effectively. See full prescribing information for ZEMPLAR.
ZEMPLAR (paricalcitol) injection, for intravenous use
Initial U.S. Approval: 1998

1 INDICATIONS AND USAGE

ZEMPLAR is a vitamin D analog indicated for the prevention and treatment of secondary hyperparathyroidism in patients 5 years of age and older with chronic kidney disease on dialysis (1).

2 DOSAGE AND ADMINISTRATION

- Ensure serum calcium is not above the upper limit of normal before initiating (2.1)
- Administer ZEMPLAR intravenously through a hemodialysis vascular access at any time during dialysis (2.1).

Adult Dose:

- Initiate at 0.04 mcg/kg to 0.1 mcg/kg (2.8 mcg to 7 mcg) no more frequently than every other day (2.2).
- Target maintenance dose to intact parathyroid hormone (PTH) levels within the desired therapeutic range and serum calcium within normal limits (2.2).
- Monitor serum calcium frequently (e.g., twice weekly) and intact PTH levels every 2 to 4 weeks after dose initiation or adjustment (2.2).
- See Table 1 in the full prescribing information for titration recommendations based upon intact PTH levels (2.2).
- Suspend or decrease the dose for persistent abnormally low intact PTH or serum calcium consistently above the normal range (2.2).

Pediatric Dose:

- Initiate ZEMPLAR as an intravenous bolus dose of:
  ○ 0.04 mcg/kg if baseline intact PTH is less than 500 pg/mL, or
  ○ 0.08 mcg/kg if baseline intact PTH is 500 pg/mL or greater (2.3)
- Target maintenance dose to intact PTH levels within the desired therapeutic range and serum calcium within normal limits (2.3).
- Monitor serum calcium frequently (e.g., twice weekly) and intact PTH levels every 2 to 4 weeks after dose initiation or adjustment (2.3).
- See Table 2 in the full prescribing information for titration recommendations based upon intact PTH levels (2.3).
- Suspend or decrease the dose for persistent abnormally low intact PTH or serum calcium consistently above the normal range (2.3).

3 DOSAGE FORMS AND STRENGTHS

ZEMPLAR is available as (3):

- Injection: 2 mcg/mL single-dose vial
- Injection: 5 mcg/mL single-dose vial
- Injection: 10 mcg/2 mL (5 mcg/mL) multiple-dose vial

4 CONTRAINDICATIONS

- Hypercalcemia (4)
- Vitamin D toxicity (4)
- Known hypersensitivity to paricalcitol or any inactive ingredient (4).

5 WARNINGS AND PRECAUTIONS

- Hypercalcemia: Can occur during treatment with ZEMPLAR and can lead to cardiac arrhythmias and seizures. Severe hypercalcemia may require emergency attention. The risk may be increased when ZEMPLAR is used concomitantly with high dose calcium preparations, thiazide diuretics, or vitamin D compounds. Inform patients about symptoms of hypercalcemia and monitor serum calcium prior to initiation and during treatment and adjust dose accordingly (2, 5.1).
- Digitalis toxicity: Risk increases with hypercalcemia. In patients using digitalis compounds, monitor both serum calcium and patients for signs and symptoms of digitalis toxicity. Monitor more frequently when initiating or adjusting the dose of ZEMPLAR (5.2).
- Adynamic Bone Disease: May develop and increase risk of fractures if intact PTH levels are suppressed to abnormally low levels. Monitor intact PTH levels and adjust dose if needed (5.3).

6 ADVERSE REACTIONS

The most common adverse reactions (> 5% and more frequent than placebo) are nausea, vomiting and edema (6.1).

To report SUSPECTED ADVERSE REACTIONS, contact AbbVie Inc. at 1-800-633-9110 or FDA at 1-800-FDA-1088 or www.fda.gov/medwatch.

7 DRUG INTERACTIONS

Strong CYP3A Inhibitors: Co-administration with strong CYP3A inhibitors (e.g., ketoconazole) increases ZEMPLAR exposure. Dose adjustment may be necessary. Closely monitor intact PTH and serum calcium (2.4, 7).

FULL PRESCRIBING INFORMATION

1 INDICATIONS AND USAGE

ZEMPLAR is indicated for the prevention and treatment of secondary hyperparathyroidism in patients 5 years of age and older with chronic kidney disease (CKD) on dialysis.

2 DOSAGE AND ADMINISTRATION

2.1 Important Administration Information

- Ensure serum calcium is not above the upper limit of normal before initiating treatment [see Warnings and Precautions (5.1)].
- Administer ZEMPLAR intravenously through a hemodialysis vascular access port at any time during dialysis. ZEMPLAR may be administered intravenously if an access port is unavailable.
- Inspect ZEMPLAR visually prior to administration; the solution should appear clear and colorless. Do not use if the solution is not clear or particles are present.
- Discard unused portion of 2 mcg/mL and 5 mcg/mL single-dose vials.

2.2 Starting Dose and Dose Titration in Adults

- Initiate ZEMPLAR as an intravenous bolus dose of 0.04 mcg/kg to 0.1 mcg/kg (2.8 mcg to 7 mcg) no more frequently than every other day at any time during dialysis.
- Target the maintenance dose of ZEMPLAR to intact parathyroid hormone (PTH) levels within the desired therapeutic range and serum calcium within normal limits.
- Monitor serum calcium frequently (e.g., twice weekly) and intact PTH levels every 2 to 4 weeks after initiation of therapy or dose adjustment.
- Titrate the dose of ZEMPLAR based on intact PTH (see Table 1). Prior to raising the dose, ensure serum calcium is within normal limits. The maximum daily adult dose is 0.24 mcg/kg.
- Suspend or decrease the dose if intact PTH is persistently and abnormally low to reduce the risk of adynamic bone disease [see Warnings and Precautions (5.3)] or if serum calcium is consistently above the normal range to reduce the risk of hypercalcemia [see Warnings and Precautions (5.1)]. If dose suspension is necessary, restart at a reduced dose after laboratory values have normalized.

Table 1. Recommended ZEMPLAR Adult Dose Titration Based Upon intact PTH
Intact PTH Level At Follow-up Visit | Dosage Adjustment
Above target and intact PTH increased | Increase* by 2 mcg to 4 mcg every 2 to 4 weeks
Above target and intact PTH decreased by less than 30% | Increase* by 2 mcg to 4 mcg every 2 to 4 weeks
Above target and intact PTH decreased by 30% to 60% | No Change
Above target and intact PTH decreased by more than 60% | Decrease per clinical judgement
At target and intact PTH stable | No Change
* The maximum daily adult dose is 0.24 mcg/kg

2.3 Starting Dose and Dose Titration for Pediatric Patients 5 Years of Age and Above

- Initiate ZEMPLAR as an intravenous bolus dose of:
  ○ 0.04 mcg/kg if baseline intact PTH is less than 500 pg/mL, or
  ○ 0.08 mcg/kg if baseline intact PTH is 500 pg/mL or greater
- Administer ZEMPLAR three times per week, no more frequently than every other day, at any time during dialysis.
- Target the maintenance dose of ZEMPLAR to intact PTH levels within the desired therapeutic range and serum calcium within normal limits.
- Monitor serum calcium frequently (e.g., twice weekly) and intact PTH levels every 2 to 4 weeks after initiation of therapy or dose adjustment.
- Titrate the dose of ZEMPLAR based on intact PTH (see Table 2). Prior to raising the dose, ensure serum calcium is within normal limits.
- Suspend or decrease the dose if intact PTH is persistently and abnormally low to reduce the risk of adynamic bone disease [see Warnings and Precautions (5.3)] or if serum calcium is consistently above the normal range to reduce the risk of hypercalcemia [see Warnings and Precautions (5.1)]. If dose suspension is necessary, restart at a reduced dose after laboratory values have normalized.

Table 2. Recommended ZEMPLAR Pediatric Dose Titration Based Upon intact PTH – Patients 5 years of age and older
Intact PTH Level At Follow-up Visit | Dosage Adjustment
Above target and intact PTH decreased by less than 30% | Increase by 0.04 mcg/kg every 2 to 4 weeks
Intact PTH 150 pg/mL or greater and decreased by 30% to 60% | No Change
Intact PTH less than 150 pg/mL or decreased by more than 60% | Decrease by 0.04 mcg/kg weekly, or by 50% if decreased dose equals zero

2.4 Drug Interactions that May Require Dosage Adjustments of ZEMPLAR

- Increased monitoring of serum calcium and dose adjustment of ZEMPLAR may be necessary when given concomitantly with drugs that may increase the risk of hypercalcemia [see Drug Interactions (7)].
- Increased monitoring of both serum calcium and intact PTH as well as dose adjustment of ZEMPLAR may be necessary when given concomitantly with strong CYP3A inhibitors [see Drug Interactions (7)].

3 DOSAGE FORMS AND STRENGTHS

Injection: clear, colorless solution available as follows:

- 2 mcg/mL single-dose vial
- 5 mcg/mL single-dose vial
- 10 mcg/2 mL (5 mcg/mL) multiple-dose vial

4 CONTRAINDICATIONS

ZEMPLAR is contraindicated in patients with:

- Hypercalcemia [see Warnings and Precautions (5.1)]
- Vitamin D toxicity [see Warnings and Precautions (5.1)]
- Known hypersensitivity to paricalcitol or any of the inactive ingredients in ZEMPLAR. Hypersensitivity adverse reactions have been reported [e.g., angioedema (including laryngeal edema) and urticaria] [see Adverse Reactions (6.2)].

5 WARNINGS AND PRECAUTIONS

5.1 Hypercalcemia

Hypercalcemia may occur during ZEMPLAR treatment. Acute hypercalcemia may increase the risk of cardiac arrhythmias and seizures and may potentiate the effect of digitalis on the heart [see Warnings and Precautions (5.2)]. Chronic hypercalcemia can lead to generalized vascular calcification and other soft-tissue calcification. Severe hypercalcemia may require emergency attention.

Hypercalcemia may be exacerbated by concomitant administration of high doses of calcium-containing preparations, thiazide diuretics, or other vitamin D compounds [see Drug Interactions (7)]. In addition, high intake of calcium and phosphate concomitantly with vitamin D compounds may lead to hypercalciuria and hyperphosphatemia. Patients with a history of hypercalcemia prior to initiating therapy may be at increased risk for development of hypercalcemia with ZEMPLAR. In these circumstances, frequent serum calcium monitoring and ZEMPLAR dose adjustments may be required.

When initiating ZEMPLAR or adjusting ZEMPLAR dose, measure serum calcium frequently (e.g., twice weekly). Once a maintenance dose has been established, measure serum calcium at least monthly. If hypercalcemia occurs, reduce the dose or discontinue ZEMPLAR until serum calcium is normal [see Dosage and Administration (2.2, 2.3)].

Inform patients about the symptoms of elevated calcium (feeling tired, difficulty thinking clearly, loss of appetite, nausea, vomiting, constipation, increased thirst, increased urination and weight loss) and instruct them to report new or worsening symptoms when they occur.

5.2 Digitalis Toxicity

ZEMPLAR can cause hypercalcemia [see Warnings and Precautions (5.1)] which increases the risk of digitalis toxicity. In patients using ZEMPLAR concomitantly with digitalis compounds, monitor serum calcium and patients for signs and symptoms of digitalis toxicity. Increase the frequency of monitoring when initiating or adjusting the dose of ZEMPLAR [see Drug Interactions (7)].

5.3 Adynamic Bone Disease

Adynamic bone disease with subsequent increased risk of fractures may develop if intact PTH levels are suppressed by ZEMPLAR to abnormally low levels. Monitor intact PTH levels to avoid over suppression and adjust ZEMPLAR dose, if needed [see Dosage and Administration (2.2, 2.3)].

6 ADVERSE REACTIONS

The following serious adverse reactions are described below and elsewhere in the labeling:

- Hypercalcemia [see Warnings and Precautions (5.1)]
- Adynamic Bone Disease [see Warnings and Precautions (5.3)]

6.1 Clinical Trials Experience

Because clinical studies are conducted under widely varying conditions, adverse reaction rates observed in the clinical studies of a drug cannot be directly compared to rates in the clinical studies of another drug and may not reflect the rates observed in practice.

Four placebo-controlled, double-blind, multicenter studies were conducted in 113 patients (51% male, 10% Caucasian, 81% African-American and 9% Hispanic, ranging in age from 18 to 90 years). Sixty-two patients were exposed to ZEMPLAR and the average dose at the end of treatment was 0.12 mcg/kg/dose with a mean number of 55 days of dosing across the studies. Discontinuation of therapy due to any adverse reaction occurred in 6.5% of patients treated with ZEMPLAR and 2.0% of patients treated with placebo. Adverse reactions occurring with greater frequency in the ZEMPLAR group and at a frequency of 2% or greater are presented in Table 3.

Table 3. Adverse Reactions Occurring at a Rate of 2% or Greater in Patients with CKD on Dialysis in Four Placebo-Controlled Studies
Adverse Reaction | Placebo (n = 51) % | ZEMPLAR (n = 62) %
Nausea | 8 | 13
Vomiting | 6 | 8
Edema | 0 | 7
Gastrointestinal Hemorrhage | 2 | 5
Chills | 2 | 5
Pyrexia | 2 | 5
Pneumonia | 0 | 5
Sepsis | 2 | 5
Influenza | 4 | 5
Arthralgia | 4 | 5
Palpitations | 0 | 3
Dry Mouth | 2 | 3
Malaise | 0 | 3

Other Adverse Reactions

The following adverse reactions occurred in less than 2% of the ZEMPLAR treated patients in the above mentioned studies and in additional double-blind, active-controlled and open-label studies:

Blood and Lymphatic System Disorders: Anemia, lymphadenopathy

Cardiac Disorders: Arrhythmia, atrial flutter, irregular heart rate, cardiac arrest, chest discomfort, chest pain, edema peripheral

Ear and Labyrinth Disorders: Ear discomfort

Endocrine Disorders: Hypoparathyroidism

Eye Disorders: Conjunctivitis, glaucoma, ocular hyperemia

Gastrointestinal Disorders: Abdominal discomfort, constipation, diarrhea, dysphagia, gastritis, intestinal ischemia, rectal hemorrhage

General Disorders: Asthenia, condition aggravated, fatigue, feeling abnormal, pain, swelling

Infections: Nasopharyngitis, upper respiratory tract infection, vaginal infection

Injection site reactions: Injection site extravasation, injection site pain

Laboratory abnormalities: Hypercalcemia, hyperkalemia, hyperphosphatemia, hypocalcemia, increased aspartate aminotransferase, prolonged bleeding time

Metabolism and Nutrition Disorders: Decreased appetite, thirst, decreased weight

Musculoskeletal and Connective Tissue Disorders: Joint stiffness, muscle twitching, myalgia

Neoplasms Benign, Malignant and Unspecified: Breast cancer

Nervous System Disorders: Cerebrovascular accident, dizziness, dysgeusia, headache, hypoesthesia, myoclonus, paresthesia, syncope, unresponsive to stimuli, gait disturbance

Psychiatric Disorders: Agitation, confusional state, delirium, insomnia, nervousness, restlessness

Reproductive System and Breast Disorders: Breast pain, erectile dysfunction

Respiratory, Thoracic and Mediastinal Disorders: Cough, dyspnea, orthopnea, pulmonary edema, wheezing

Skin and Subcutaneous Tissue Disorders: Alopecia, blister, hirsutism, night sweats, rash pruritic, pruritus, skin burning sensation

Vascular Disorders: Hypertension, hypotension

6.2 Postmarketing Experience

The following adverse reactions have been identified during post-approval use of ZEMPLAR. Because these reactions are reported voluntarily from a population of uncertain size, it is not always possible to reliably estimate their frequency or establish a causal relationship to drug exposure.

Allergic reactions, such as rash, urticaria, and angioedema (including laryngeal edema) have been reported.

7 DRUG INTERACTIONS

Table 4 includes clinically significant drug interactions with ZEMPLAR.

Table 4. Clinically Significant Drug Interactions with ZEMPLAR
Drugs that May Increase the risk of Hypercalcemia
Clinical Impact | Concomitant administration of high doses of calcium-containing preparations or other vitamin D compounds may increase the risk of hypercalcemia. Thiazide diuretics are known to induce hypercalcemia by reducing excretion of calcium in the urine.
Examples | Calcium-containing products, other vitamin D compounds or thiazide diuretics
Intervention | Monitor calcium more frequently and adjust ZEMPLAR dose as needed [see Warnings and Precautions (5.1)].
Digitalis Compounds
Clinical Impact | ZEMPLAR can cause hypercalcemia which can potentiate the risk of digitalis toxicity.
Intervention | Monitor patients for signs and symptoms of digitalis toxicity and increase frequency of serum calcium monitoring when initiating or adjusting the dose of ZEMPLAR in patients receiving digitalis compounds [see Warnings and Precautions (5.2)].
Strong CYP3A Inhibitors
Clinical Impact | ZEMPLAR is partially metabolized by CYP3A. Exposure of ZEMPLAR will increase upon coadministration with strong CYP3A inhibitors [see Clinical Pharmacology (12.3)].
Examples | Boceprevir, clarithromycin, conivaptan, grapefruit juice, indinavir, itraconazole, ketoconazole, lopinavir/ritonavir, mibefradil, nefazodone, nelfinavir, posaconazole, ritonavir, saquinavir, telithromycin, and voriconazole
Intervention | If a patient initiates or discontinues therapy with a strong CYP3A4 inhibitor, dose adjustment of ZEMPLAR may be necessary. Monitor intact PTH and serum calcium concentrations closely.

8 USE IN SPECIFIC POPULATIONS

8.1 Pregnancy

Risk Summary

Limited data with ZEMPLAR in pregnant women are insufficient to inform a drug-associated risk for major birth defects and miscarriage. There are risks to the mother and fetus associated with chronic kidney disease in pregnancy (see Clinical Considerations).

In animal reproduction studies, slightly increased embryofetal loss was observed in pregnant rats and rabbits administered paricalcitol intravenously during the period of organogenesis at doses 2 and 0.5 times, respectively, a human dose of 14 mcg (equivalent to 0.24 mcg/kg), based on body surface area (mcg/m^2). Adverse reproductive outcomes were observed at doses that caused maternal toxicity (see Data).

The estimated background risk of major birth defects and miscarriage for the indicated population is unknown. In the U.S. general population, the estimated background risk of major birth defects and miscarriage in clinically recognized pregnancies is 2% to 4% and 15% to 20%, respectively.

Clinical Considerations

Disease-Associated Maternal and/or Embryo/Fetal Risk

Chronic kidney disease in pregnancy increases the risk for maternal hypertension and preeclampsia, miscarriage, preterm delivery, polyhydramnios, still birth, and low birth weight infants.

Data

Animal Data

Pregnant rats and rabbits were treated with paricalcitol by once-daily intravenous injection during the period of organogenesis (in rats, from gestation day (GD) 6 to 17; in rabbits, from GD 6 to 18). Rats were dosed at 0, 0.3, 1 or 3 mcg/kg/day and rabbits at 0, 0.03, 0.1 or 0.3 mcg/kg/day, representing up to 2 or 0.5 times, respectively, a human dose of 0.24 mcg/kg, based on body surface area (mcg/m^2). Slightly decreased fetal viability was observed in both studies at the highest doses representing 2 and 0.5 times, respectively, a human dose of 0.24 mcg/kg, in the presence of maternal toxicity (decreased body weight and food consumption). Pregnant rats were administered paricalcitol by intravenous injection three times per week at doses of 0, 0.3, 3 or 20 mcg/kg/day throughout gestation, parturition and lactation (GD 6 to lactation day (LD) 20) representing exposures up to 13 times a human dose of 0.24 mcg/kg. A small increase in stillbirths and pup deaths from parturition to LD 4 were observed at the high dose when compared to the control group (9.2% versus 3.3% in controls) at 13 times a human dose of 0.24 mcg/kg, which occurred at a maternally toxic dose known to cause hypercalcemia in rats. Surviving pups were not adversely affected; body weight gains, developmental landmarks, reflex ontogeny, learning indices, and locomotor activity were all within normal parameters. F1 reproductive capacity was unaffected.

8.2 Lactation

Risk Summary

There is no information available on the presence of paricalcitol in human milk, the effects of the drug on the breastfed infant or the effects of the drug on milk production. Studies in rats have shown that paricalcitol and/or its metabolites are present in the milk of lactating rats. When a drug is present in animal milk, it is likely that the drug will be present in human milk (see Data). Infants exposed to ZEMPLAR through breast milk should be monitored for signs and symptoms of hypercalcemia (see Clinical Considerations). The developmental and health benefits of breastfeeding should be considered along with the mother’s clinical need for ZEMPLAR and any potential adverse effects on the breast-fed child from ZEMPLAR or from the underlying maternal condition.

Clinical Considerations

Infants exposed to ZEMPLAR through breast milk should be monitored for signs and symptoms of hypercalcemia, including seizures, vomiting, constipation and weight loss. Monitoring of serum calcium in the infant should be considered.

Data

Following a single oral administration of 20 mcg/kg of radioactive [^3H] paricalcitol to lactating rats, the concentrations of total radioactivity was determined. Lower levels of total radioactivity were present in the milk compared to that in the plasma of the dams indicating that low levels of [^3H] paricalcitol and/or its metabolites are secreted into milk. Exposure of the pups to [^3H] paricalcitol through milk was confirmed by the presence of radioactive material in the pups’ stomachs.

8.4 Pediatric Use

The safety and efficacy of ZEMPLAR for the prevention and treatment of secondary hyperparathyroidism associated with CKD have been established in pediatric patients 5 years of age and older with CKD on dialysis. Use of ZEMPLAR in pediatric patients 5 years of age and older is supported by evidence from an adequate and well-controlled study in 29 patients, 5 to 19 years of age, with CKD on hemodialysis [see Clinical Studies (14)].

The safety and efficacy of ZEMPLAR have not been established in pediatric patients less than 5 years old.

8.5 Geriatric Use

Clinical studies of ZEMPLAR did not include sufficient numbers of subjects aged 65 and over to determine whether they respond differently from younger subjects. Other reported clinical experience has not identified differences in responses between the elderly and younger patients. In general, dose selection for an elderly patient should be cautious, usually starting at the low end of the dosing range, reflecting the greater frequency of decreased hepatic or cardiac function, and of concomitant disease or other drug therapy.

8.6 Hepatic Impairment

The pharmacokinetics of ZEMPLAR were studied in patients with mild and moderate hepatic impairment and were similar to that of patients with normal hepatic function. No dose adjustment is required in patients with mild or moderate hepatic function.

ZEMPLAR has not been studied in patients with severe hepatic impairment.

10 OVERDOSAGE

Overdosage of ZEMPLAR may lead to hypercalcemia, hypercalciuria, and hyperphosphatemia. [see Warnings and Precautions (5.1)].

The treatment of acute overdosage should consist of supportive measures and discontinuation of drug administration. Serum calcium levels should be measured until normal.

Paricalcitol is not significantly removed by dialysis.

11 DESCRIPTION

Paricalcitol, USP, is a synthetically manufactured active vitamin D analog. It is a white powder chemically designated as 19-nor-1α,3β,25-trihydroxy-9,10-secoergosta-5(Z),7(E),22(E)-triene and has the following structural formula:

Molecular formula is C27H44O3.

Molecular weight is 416.64.

ZEMPLAR (paricalcitol) injection is a sterile, clear, colorless, aqueous solution for intravenous use. Each mL contains paricalcitol, 2 mcg or 5 mcg and the following inactive ingredients: alcohol, 20% (v/v) and propylene glycol, 30% (v/v).

12 CLINICAL PHARMACOLOGY

12.1 Mechanism of Action

Paricalcitol is a synthetic, biologically active vitamin D2 analog. Preclinical and in vitro studies have demonstrated that paricalcitol's biological actions are mediated through binding of the vitamin D receptor (VDR), which results in the selective activation of vitamin D responsive pathways. Vitamin D and paricalcitol have been shown to reduce PTH levels by inhibiting PTH synthesis and secretion.

12.3 Pharmacokinetics

Within two hours after administering ZEMPLAR intravenous doses ranging from 0.04 to 0.24 mcg/kg, concentrations of paricalcitol decreased rapidly; thereafter, concentrations of paricalcitol declined log-linearly. No accumulation of paricalcitol was observed with three times a week dosing.

Distribution

Paricalcitol is extensively bound to plasma proteins (≥99.8%). In healthy subjects, the steady state volume of distribution is approximately 23.8 L. The mean volume of distribution following a 0.24 mcg/kg dose of paricalcitol in CKD Stage 5 subjects requiring hemodialysis (HD) and peritoneal dialysis (PD) is between 31 and 35 L.

Elimination

Metabolism

After intravenous administration of a 0.48 mcg/kg dose of ^3H-paricalcitol, parent drug was extensively metabolized, with only about 2% of the dose eliminated unchanged in the feces and no parent drug found in the urine. Several metabolites were detected in both the urine and feces. Most of the systemic exposure was from the parent drug. Two minor metabolites, relative to paricalcitol, were detected in human plasma. One metabolite was identified as 24(R)-hydroxy paricalcitol, while the other metabolite was unidentified. The 24(R)-hydroxy paricalcitol is less active than paricalcitol in an in vivo rat model of PTH suppression.

In vitro data suggest that paricalcitol is metabolized by multiple hepatic and non-hepatic enzymes, including mitochondrial CYP24, as well as CYP3A4 and UGT1A4. The identified metabolites include the product of 24(R)-hydroxylation (present at low levels in plasma), as well as 24,26- and 24,28-dihydroxylation and direct glucuronidation.

Excretion

Paricalcitol is excreted primarily by hepatobiliary excretion. Approximately 63% of the radioactivity was eliminated in the feces and 19% was recovered in the urine in healthy subjects. In healthy subjects, the mean elimination half-life of paricalcitol is about five to seven hours over the studied dose range of 0.04 to 0.16 mcg/kg. The pharmacokinetics of paricalcitol has been studied in CKD patients requiring hemodialysis (HD) and peritoneal dialysis (PD). The mean elimination half-life of paricalcitol after administration of 0.24 mcg/kg paricalcitol IV bolus dose in CKD HD and PD patients is 13.9 and 15.4 hours, respectively (Table 5).

Table 5. Mean ± SD Paricalcitol Pharmacokinetic Parameters in CKD Patients on Dialysis Following Single 0.24 mcg/kg Intravenous Bolus Dose
 | CKD -HD (n=14) | CKD -PD (n=8)
Cmax (ng/mL) | 1.680 ± 0.511 | 1.832 ± 0.315
AUC0-∞ (ng·h/mL) | 14.51 ± 4.12 | 16.01 ± 5.98
β (1/h) | 0.050 ± 0.023 | 0.045 ± 0.026
t1/2 (h)* | 13.9 ± 7.3 | 15.4 ± 10.5
CL (L/h) | 1.49 ± 0.60 | 1.54 ± 0.95
Vdβ (L) | 30.8 ± 7.5 | 34.9 ± 9.5
* harmonic mean ± pseudo standard deviation, HD: hemodialysis, PD: peritoneal dialysis. The degree of accumulation was consistent with the half-life and dosing frequency.

Specific Populations

The pharmacokinetics of paricalcitol has not been investigated in geriatric and pediatric patients.

Male and Female Patients

The pharmacokinetics of paricalcitol were gender independent.

Patients with Hepatic Impairment

The disposition of paricalcitol (0.24 mcg/kg) was compared in patients with mild (n=5) and moderate (n=5) hepatic impairment (as indicated by the Child-Pugh method) and subjects with normal hepatic function (n=10). The pharmacokinetics of unbound paricalcitol were similar across the range of hepatic function evaluated in this study. The influence of severe hepatic impairment on the pharmacokinetics of paricalcitol has not been evaluated.

Patients with Renal Impairment

The pharmacokinetics of paricalcitol have been studied in CKD patients requiring hemodialysis (HD) and peritoneal dialysis (PD). Hemodialysis procedure has essentially no effect on paricalcitol elimination. However, compared to healthy subjects, CKD patients on dialysis showed a decreased CL and increased half-life.

Drug Interaction Studies

An in vitro study indicates that paricalcitol is not an inhibitor of CYP1A2, CYP2A6, CYP2B6, CYP2C8, CYP2C9, CYP2C19, CYP2D6, CYP2E1, or CYP3A at concentrations up to 50 nM (21 ng/mL) (approximately 20-fold greater than that obtained after highest tested dose). In fresh primary cultured hepatocytes, the induction observed at paricalcitol concentrations up to 50 nM was less than two-fold for CYP2B6, CYP2C9 or CYP3A, where the positive controls rendered a six- to nineteen-fold induction. Hence, paricalcitol is not expected to inhibit or induce the clearance of drugs metabolized by these enzymes.

Drug interactions with paricalcitol injection have not been studied. The following studies have been performed with oral paricalcitol capsules.

Omeprazole

The pharmacokinetic interaction between paricalcitol capsule (16 mcg) and omeprazole (40 mg; oral), a strong inhibitor of CYP2C19, was investigated in a single dose, crossover study in healthy subjects. The pharmacokinetics of paricalcitol were unaffected when omeprazole was administrated approximately 2 hours prior to the paricalcitol dose.

Strong CYP3A Inhibitors

Ketoconazole

The effect of multiple doses of ketoconazole, a strong inhibitor of CYP3A administered as 200 mg BID for 5 days, on the pharmacokinetics of paricalcitol capsule has been studied in healthy subjects. The Cmax of paricalcitol was minimally affected, but AUC0-∞ approximately doubled in the presence of ketoconazole. The mean half-life of paricalcitol was 17.0 hours in the presence of ketoconazole as compared to 9.8 hours, when paricalcitol was administered alone [see Drug Interactions (7)].

13 NONCLINICAL TOXICOLOGY

13.1 Carcinogenesis, Mutagenesis and Impairment of Fertility

In a 104-week carcinogenicity study in CD-1 mice, an increased incidence of uterine leiomyoma and leiomyosarcoma was observed at subcutaneous doses of 1, 3, 10 mcg/kg administered 3 times per week (2 to 15 times the AUC at a human dose of 14 mcg, equivalent to 0.24 mcg/kg based on AUC). The incidence rate of uterine leiomyoma was significantly different than the control group at the highest dose of 10mcg/kg.

In a 104-week carcinogenicity study in rats, there was an increased incidence of benign adrenal pheochromocytoma at subcutaneous doses of 0.15, 0.5, 1.5 mcg/kg administered 3 times per week (at less than clinical exposure to 7 times the exposure following a human dose of 14 mcg, equivalent to 0.24 mcg/kg based on AUC). The increased incidence of pheochromocytomas in rats may be related to the alteration of calcium homeostasis by paricalcitol.

Paricalcitol did not exhibit genetic toxicity in vitro with or without metabolic activation in the microbial mutagenesis assay (Ames Assay), mouse lymphoma mutagenesis assay (L5178Y), or a human lymphocyte cell chromosomal aberration assay. There was also no evidence of genetic toxicity in an in vivo mouse micronucleus assay.

Paricalcitol had no effect on fertility (male or female) in rats at intravenous doses up to 20 mcg/kg/dose (13 times a human dose of 14 mcg, equivalent to 0.24 mcg/kg based on surface area, mcg/m^2).

14 CLINICAL STUDIES

Adult Studies in CKD on Dialysis

Three 12-week, placebo-controlled studies were conducted in 78 patients with CKD on hemodialysis. In these studies, patients ranged in age from 22 to 90 years, 51% were males, 13% were Caucasian, 79% were African-American, and 8% were Hispanic. The most common causes of renal failure were hypertension and diabetes. The dose of ZEMPLAR was started at 0.04 mcg/kg 3 times per week intravenously. The dose was increased by 0.04 mcg/kg every 2 weeks until intact PTH levels were decreased at least 30% from baseline or a fifth escalation brought the dose to 0.24 mcg/kg, or intact PTH fell to less than 100 pg/mL, or the Ca × P product was greater than 75 within any 2 week period, or serum calcium became greater than 11.5 mg/dL at any time.

Patients treated with ZEMPLAR achieved a mean intact PTH reduction of 30% within 6 weeks. The results from these studies are as follows:

Table 6. Mean Changes from Baseline to Final Evaluation in intact PTH, Alkaline Phosphatase, Phosphorus and Calcium × Phosphorus Product in Adult Patients with CKD on Dialysis in Three 12-Week Placebo-Controlled Studies
 | Group (No. of Pts.) | Baseline Mean (Range) | Mean (SE) Change From Baseline to Final Evaluation
intact PTH (pg/mL) | ZEMPLAR (n = 40) | 783 (291 – 2076) | -379 (43.7)
 | placebo (n = 38) | 745 (320 – 1671) | -69.6 (44.8)
Alkaline Phosphatase (U/L) | ZEMPLAR (n = 31) | 150 (40 – 600) | -41.5 (10.6)
 | placebo (n = 34) | 169 (56 – 911) | +2.6 (10.1)
Phosphorus (mg/dL) | ZEMPLAR (n = 40) | 5.8 (3.7 – 10.2) | +0.47 (0.3)
 | placebo (n = 38) | 6.0 (2.8 – 8.8) | -0.47 (0.3)
Calcium × Phosphorus Product | ZEMPLAR (n = 40) | 54 (32 – 106) | +7.9 (2.2)
 | placebo (n = 38) | 54 (26 – 77) | -3.9 (2.3)

Pediatric Study in CKD on Dialysis

ZEMPLAR was evaluated in a 12-week randomized, double-blind, placebo-controlled study of 29 pediatric patients, aged 5 to 19 years, with CKD on hemodialysis; nearly all had received some form of vitamin D prior to the study. Of the 29 patients, 76% were male, 52% were Caucasian and 45% were African-American. The initial dose of ZEMPLAR was 0.04 mcg/kg 3 times per week, based on baseline intact PTH level of less than 500 pg/mL, or 0.08 mcg/kg 3 times per week, based on baseline intact PTH level of 500 pg/mL or greater. The dose of ZEMPLAR was adjusted in 0.04 mcg/kg increments based on the levels of serum intact PTH, calcium and Ca × P. The mean baseline levels of intact PTH were 841 pg/mL for the 15 ZEMPLAR-treated patients and 740 pg/mL for the 14 placebo-treated patients. The mean dose of ZEMPLAR administered was 4.6 mcg (range: 0.8 mcg to 9.6 mcg). Sixty-seven percent of the ZEMPLAR-treated patients and 14% of the placebo-treated patients completed the trial. Seventy-one percent of the placebo-treated patients discontinued due to excessive elevations in intact PTH levels, as defined by 2 consecutive intact PTH levels greater than 700 pg/mL and greater than baseline after 4 weeks of treatment.

The primary efficacy analysis demonstrated that 60% of ZEMPLAR-treated patients and 21% of placebo-treated patients achieved two consecutive greater than or equal to 30% reductions from baseline in intact PTH.

16 HOW SUPPLIED/STORAGE AND HANDLING

ZEMPLAR injection is a clear, colorless solution available in cartons of 25 vials as follows:

Table 7. ZEMPLAR Presentations
Total Strength per Total Volume | Strength per mL | Total Vial Volume and Vial Type | NDC No.
2 mcg/mL | 2 mcg/mL | 1 mL single-dose vial | 0074-4637-01
5 mcg/mL | 5 mcg/mL | 1 mL single-dose vial | 0074-1658-01
10 mcg/2 mL | 5 mcg/mL | 2 mL multiple-dose vial | 0074-1658-05

Store at 25°C (77°F). Excursions permitted between 15° to 30°C (59° to 86°F).

Discard any unused portion of the single-dose vial after use.

The contents of the multiple-dose vial remain stable up to seven days after initial use when stored at controlled room temperature.

17 PATIENT COUNSELING INFORMATION

Hypercalcemia

Advise patients to contact a health care provider if they develop symptoms of elevated calcium (e.g. feeling tired, difficulty thinking clearly, loss of appetite, nausea, vomiting, constipation, increased thirst, increased urination and weight loss) [see Warnings and Precautions (5.1)].

Monitoring

Inform patients that they will need routine monitoring of laboratory parameters such as calcium and intact PTH while receiving ZEMPLAR. Inform patients that more frequent monitoring is necessary during the initiation of therapy, following dose changes or when potentially interacting medications are started or discontinued [see Dosage and Administration (2), Drug Interactions (7)].

Drug Interactions

Advise patients to inform their physician of all medications, including prescription and nonprescription drugs, and supplements they are taking. Advise patients to also inform their physician that they are receiving ZEMPLAR if a new medication is prescribed [see Drug Interactions (7)].

Manufactured for
AbbVie Inc.
North Chicago, IL 60064, U.S.A.
© 2024 AbbVie. All rights reserved.

ZEMPLAR and its design are trademarks of AbbVie Inc.

8022191 August, 2024

PACKAGE LABEL

NDC 0074–4637–01
1 mL Single-Dose Vial
Discard unused portion
Zemplar®(paricalcitol) Injection 2 mcg/mL
For Intravenous Use
Mfd for: AbbVie Inc, N. Chgo, IL 60064 USA
Rx only

PACKAGE LABEL

NDC 0074-4637-01
Single-Dose Vials - Discard unused portion
Zemplar® 2mcg/mL Rx only
(paricalcitol) Injection
For Intravenous Use
25 x 1 mL Vials abbvie

PACKAGE LABEL

NDC 0074–1658–01
1 mL Single-Dose Vial
Discard unused portion
Zemplar®(paricalcitol) Injection 5 mcg/mL
For Intravenous Use
Mfd for: AbbVie Inc., N. Chgo, IL 60064 USA
Rx only

PACKAGE LABEL

NDC 0074-1658-01
Single-Dose Vials - Discard unused portion
Zemplar® 5mcg/mL Rx only
(paricalcitol) Injection
for Intravenous use
25 x 1 mL Vials abbvie

PACKAGE LABEL

NDC 0074–1658–05
2 mL Multi-Dose Vial
Zemplar®(paricalcitol) Injection 10 mcg/2 mL (5 mcg/mL)
For Intravenous Use
Mfd for: AbbVie Inc., N. Chgo, IL 60064 USA
Rx only

PACKAGE LABEL

NDC 0074-1658-05
Multi-dose Vials Rx only
Zemplar® 10mcg/2mL
(paricalcitol) Injection (5mcg/mL)
For Intravenous Use
25 x 2 mL Vials abbvie

PACKAGE LABEL

NDC 0074-1658-05
Multiple-Dose Vials
Zemplar®
(paricalcitol) Injection
For intravenous Use
25 x 2 mL Vials
10 mcg/2mL
(5 mcg/mL)
Rx only
abbvie

PACKAGE LABEL

NDC 0074-1658-05
Multiple-Dose Vial
Zemplar®
(paricalcitol) Injection
10 mcg/2mL (5 mcg/mL)
For Intravenous Use
25 x 2 mL Vials
Rx only
abbvie

PACKAGE LABEL

NDC 0074-1658-01
Single-Dose Vials-Discard unused portion
Zemplar® 5 mcg/mL
(paricalcitol) Injection
For Intravenous Use
25 x 1 Vials
Rx only
abbVie

PACKAGE LABEL

NDC 0074-1658-01
Single-Dose Vial 1 mL
Discard unused portion
Zemplar®
(paricalcitol) Injection
5 mcg/mL
For Intravenous Use
Rx only

PACKAGE LABEL

NDC 0074-4637-01
Single-Dose Vials – Discard unused portion
Zemplar® 2 mcg/mL
(paricalcitol) Injection
For Intravenous Use
25 x 1 mL Vials
Rx only
abbvie

PACKAGE LABEL

NDC 0074-4637-01
Single-Dose Vial 1 mL
Discard unused portion
Zemplar®
(paricalcitol) Injection
2 mcg/mL
For Intravenous Use
Rx only